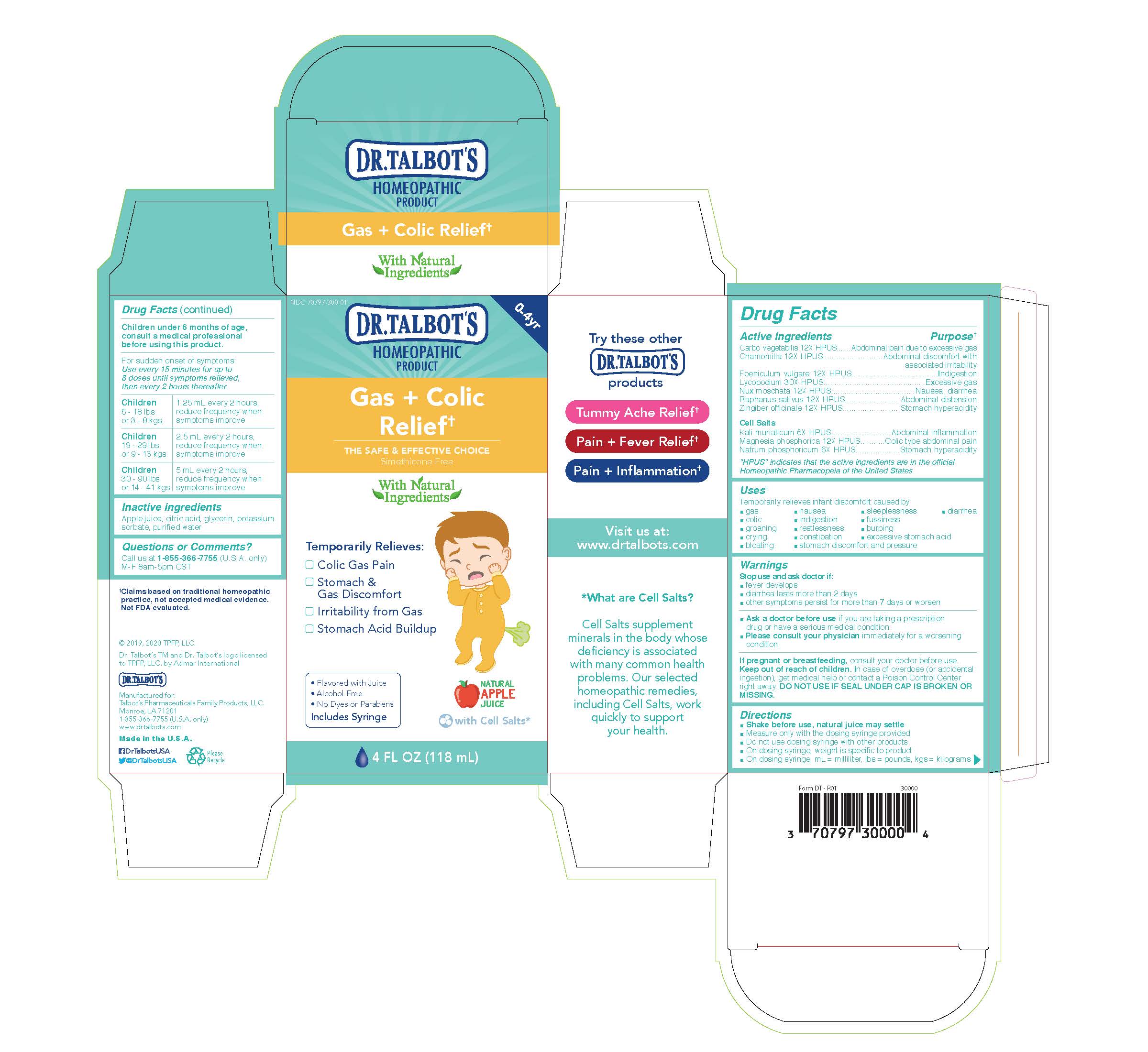 DRUG LABEL: Dr. Talbots Gas Colic Relief
NDC: 70797-310 | Form: LIQUID
Manufacturer: Talbot's Pharmaceuticals Family Products, LLC
Category: homeopathic | Type: HUMAN OTC DRUG LABEL
Date: 20211005

ACTIVE INGREDIENTS: RADISH 12 [hp_X]/118 mL; POTASSIUM CHLORIDE 6 [hp_X]/118 mL; ACTIVATED CHARCOAL 12 [hp_X]/118 mL; MATRICARIA CHAMOMILLA 12 [hp_X]/118 mL; LYCOPODIUM CLAVATUM SPORE 30 [hp_X]/118 mL; FENNEL SEED 12 [hp_X]/118 mL; NUTMEG 12 [hp_X]/118 mL; GINGER 12 [hp_X]/118 mL; SODIUM PHOSPHATE, DIBASIC, HEPTAHYDRATE 6 [hp_X]/118 mL; MAGNESIUM PHOSPHATE, DIBASIC TRIHYDRATE 12 [hp_X]/118 mL
INACTIVE INGREDIENTS: POTASSIUM SORBATE; WATER; APPLE JUICE; CITRIC ACID MONOHYDRATE; GLYCERIN

Active Ingredients

Carbo Vegetabilis 12X HPUS
Chamomilla 12X HPUS
Foeniculum Vulgare 12X HPUS
Lycopodium 30X HPUS
Nux Moschata 12X HPUS
Raphanus Sativus 12X HPUS
Zingiber Officinale 12X HPUS

Cell Salts
Kali muriaticum 6X HPUS
Magnesia phosphorica 12X HPUS
Natrum phosphoricum 6X HPUS

Purpose

Abdominal pain due to excessive gas
Abdominal discomfort with associated irritability
Indigestion
Excessive gas
Nausea, diarrhea
Abdominal distension
Stomach hyperacidity
Abdominal inflammation
Colic type abdominal pain
Stomach hyperacidity

Pregnancy or breastfeeding

If pregnant or breastfeeding, consult your doctor before use.

Keep out of reach of children. in case of overdoes (or accidental ingestion), get medical help or contact a Poison Control Center right away. DO NOT USE IF SEAL UNDER CAP IS BROKEN OR MISSING.

Directions

- Shake before use, natural juice may settle
- Measure only with the dosing syringe provided
- Do not use dosing syringe with other products
- On dosing syringe, weight is specific to product
- On dosing syringe, ml = milliliter, lbs = pounds, kgs = kilograms

Children under 6 months of age, consult a medical professional before using this product.

For sudden onset of symptoms: Use every 15 minutes for up to 8 doses until symptoms relieved, then every 2 hours thereafter.

Children 6 - 18 lbs or 3 - 8 kgs | 1.25 ml every 2 hours, reduce frequency when symptoms improve
Children 19 - 29 lbs or 9 - 13 kgs | 2.5 ml every 2 hours, reduce frequency when symptoms improve
Children 30 - 90 lbs or 14 - 41 kgs | 5 ml every 2 hours, reduce frequency when symptoms improve

Inactive ingredients

Apple juice, citric acid, glycerin, potassium sorbate, purified water

Questions

Questions or Comments?

Call us at 1-800-588-6227

M-F 8am-5pm CST

Uses

Temporarily relieves infant discomfort caused by

- gas
- colic
- groaning
- crying
- bloating
- nausea
- indigestion
- restlessness
- constipation
- stomach discomfort and pressure
- sleeplessness
- fussiness
- burping
- excessive stomach acid
- diarrhea

Warnings

Stop use and ask doctor if:

- fever develops
- diarrhea lasts more than 2 days
- other symptoms persist for more than 7 days or worsen
- Ask a doctor before use if you are taking a prescription drug or have a serious medical condition.
- Please consult your physician immediately for a worsening condition.